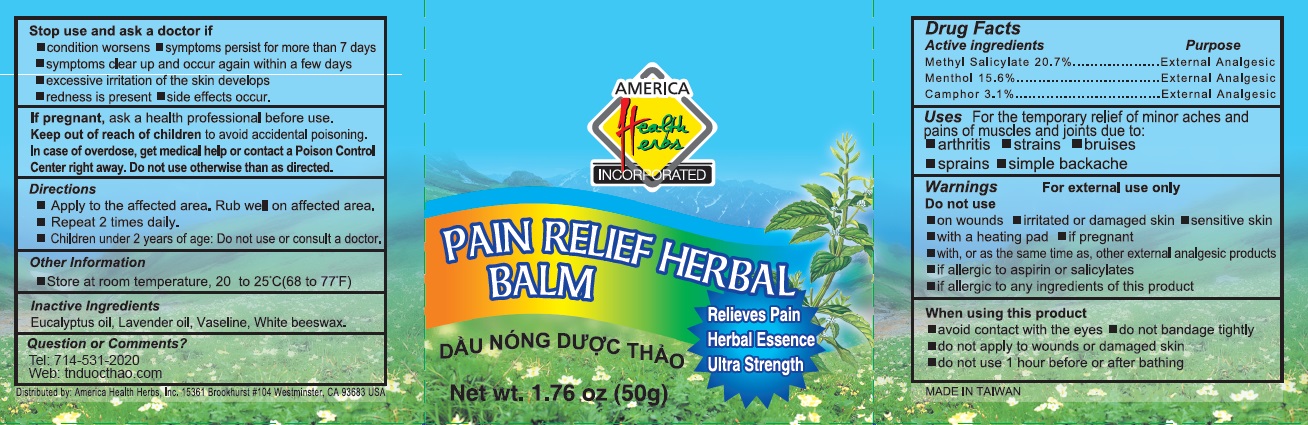 DRUG LABEL: Herbal Balm
NDC: 82198-0007 | Form: CREAM
Manufacturer: Big 5 Nutrition LLC
Category: otc | Type: HUMAN OTC DRUG LABEL
Date: 20231120

ACTIVE INGREDIENTS: MENTHOL 156 mg/1 g; METHYL SALICYLATE 207 mg/1 g; CAMPHOR (SYNTHETIC) 31 mg/1 g
INACTIVE INGREDIENTS: EUCALYPTUS OIL; LAVENDER OIL; PETROLATUM; WHITE WAX

Herbal Balm

Active Ingredients

Methyl Salicylate 20.7%

Menthol 15.6%

Camphor 3.1%

Purpose

External analgesic

Uses

For temporary relief of minor aches and pains of muscles and joints due to:

- arthritis
- strains
- bruises
- sprains
- simple backache

Warnings

For external use only

Do not use

- on wounds
- irritated or damaged skin
- sensative skin
- with a heating pad
- if pregnant
- with, or as the same time as, other external analgesic products
- if allergic to aspirin or salicylates
- if allergic to any ingredients of this prodcut

When using this product

- avoid contact with eyes
- do not bandage tightly
- do not apply to wounds or damaged skin
- do not use 1 hour before or after bathing

Stop use and ask a doctor if

- condition worsens
- symptoms persist for more than 7 days
- symptoms clear up and occur again within a few days
- excessive irritation of the skin develops
- redness is present
- side effects occur

If pregnant, ask a health professional before use.

KEEP OUT OF REACH OF CHILDREN

Keep out of reach of childrento avoid accidental poisoning

In case of overdose, get medical help or contact a Poison Control Center right away.

Do not use otherwise than as directed.

Directions

- Apply to the affected area. Rub well on affected area.
- Repeat 2 times daily.
- Children under 2 years of age: Do not use or consult a doctor.

Other Information

- Store at room temperature, 20 to 25°C (68 to 77°F)

Other Ingredients

Eucalyptus Oil, Lavender Oil, Vaseline, White beeswax.

Questions or Comments?

Tel: 714-531-2020

Web: tnduocthao.com